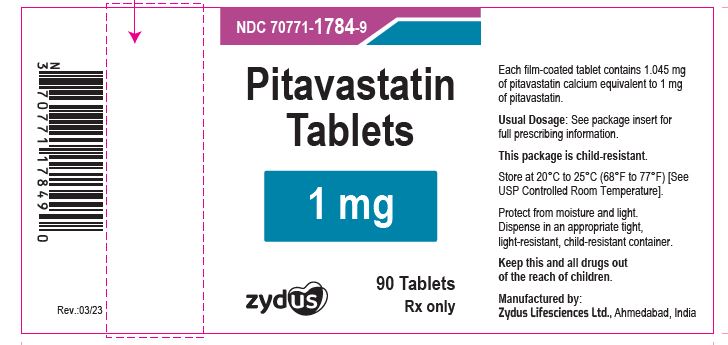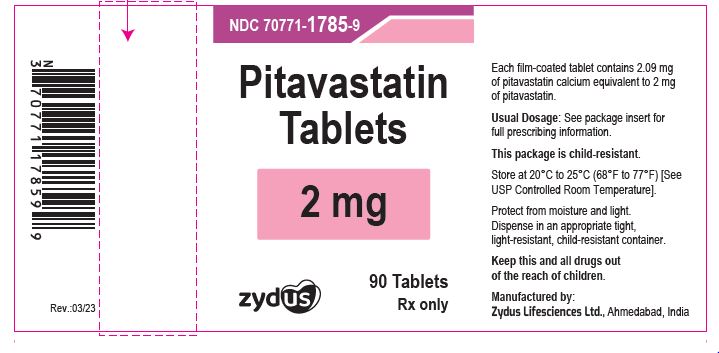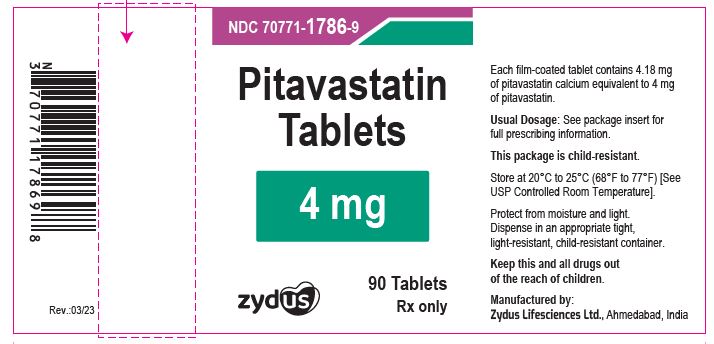 DRUG LABEL: pitavastatin calcium
NDC: 70771-1784 | Form: TABLET
Manufacturer: Zydus Lifesciences Limited
Category: prescription | Type: HUMAN PRESCRIPTION DRUG LABEL
Date: 20241203

ACTIVE INGREDIENTS: PITAVASTATIN CALCIUM 1 mg/1 1
INACTIVE INGREDIENTS: CALCIUM CARBONATE; CROSPOVIDONE (120 .MU.M); HYPROMELLOSES; LACTOSE MONOHYDRATE; MAGNESIUM STEARATE; SODIUM CARBONATE; POLYETHYLENE GLYCOL, UNSPECIFIED; TALC; TITANIUM DIOXIDE

These highlights do not include all the information needed to use PITAVASTATIN TABLETS safely and effectively. See full prescribing information for PITAVASTATIN TABLETS.
PITAVASTATIN tablets, for oral use
Initial U.S. Approval: 2009

PACKAGE LABEL.PRINCIPAL DISPLAY PANEL

Pitavastatin Tablets, 1 mg

NDC 70771-1784-9

Bottle of 90 tablets

Rx only

Pitavastatin Tablets, 2 mg

NDC 70771-1785-9

Bottle of 90 tablets

Rx only

Pitavastatin Tablets, 4 mg

NDC 70771-1786-9

Bottle of 90 tablets

Rx only